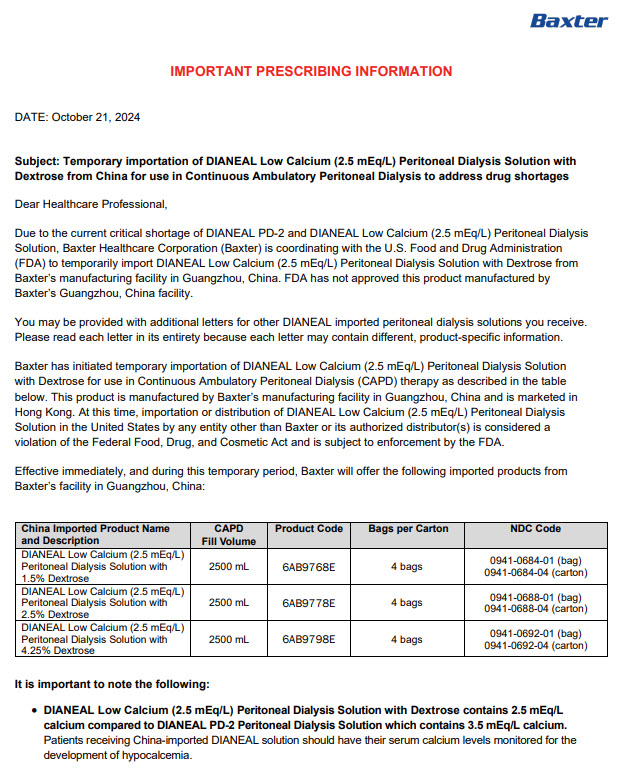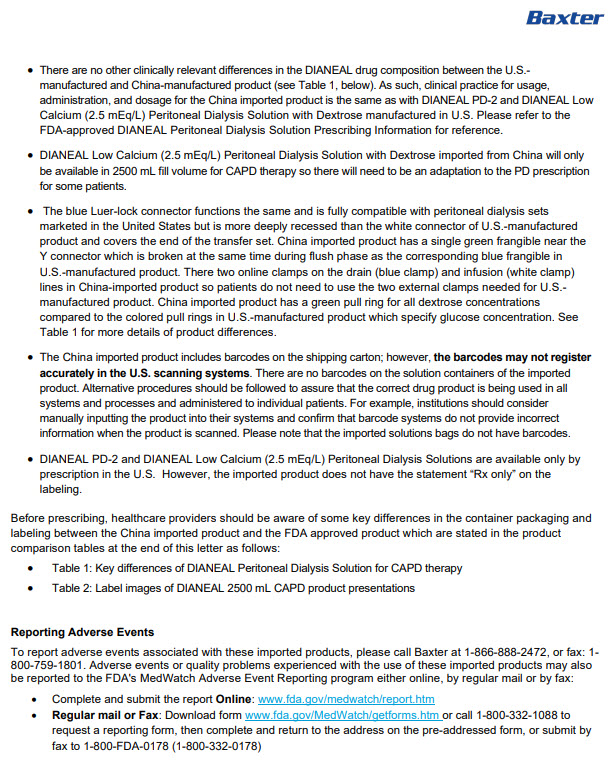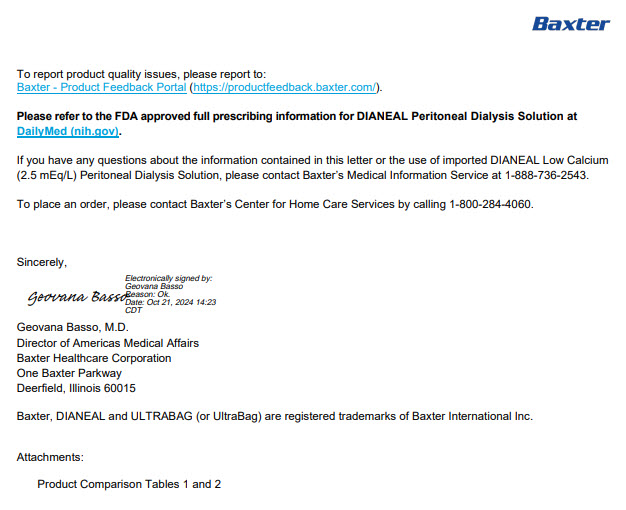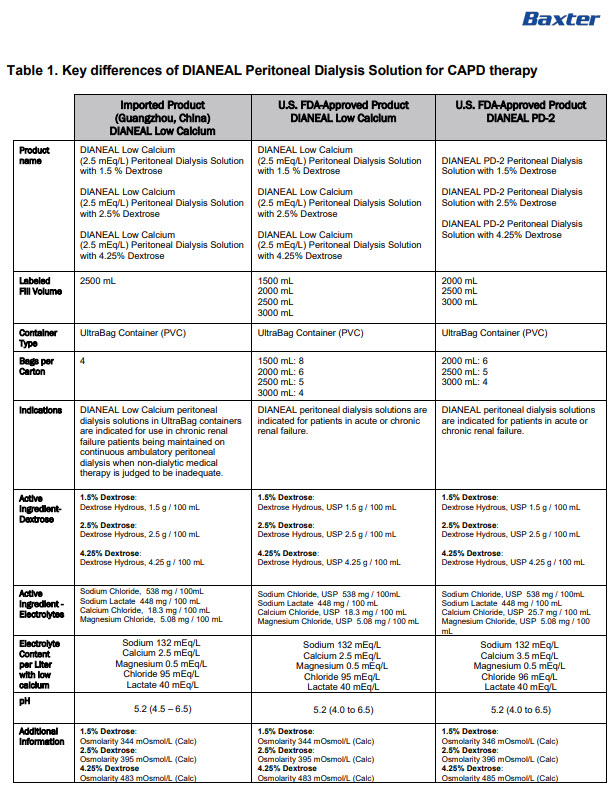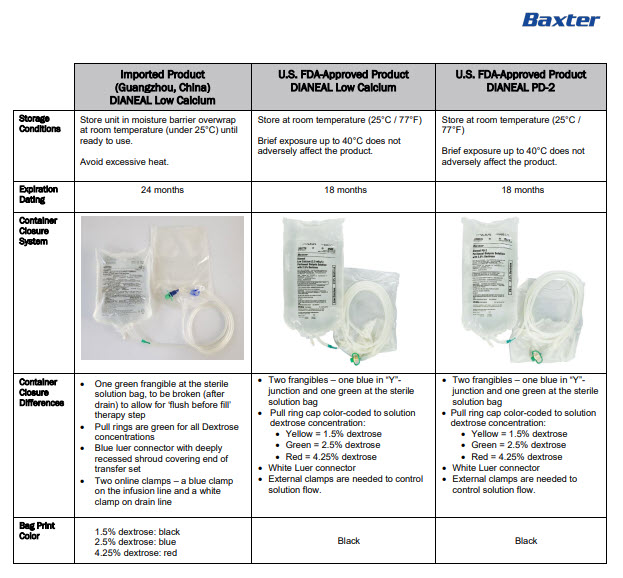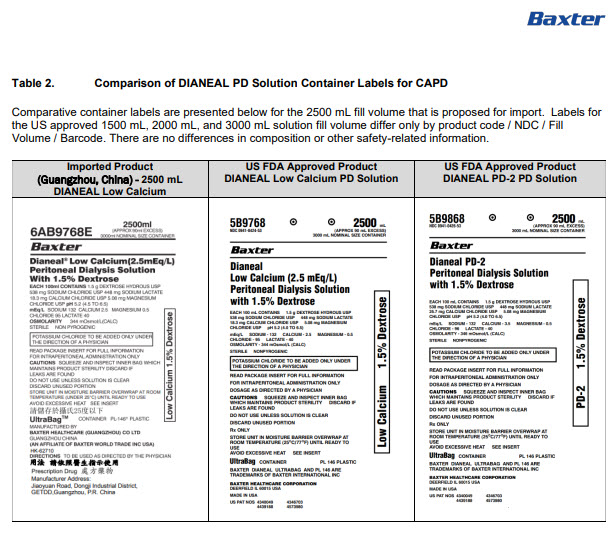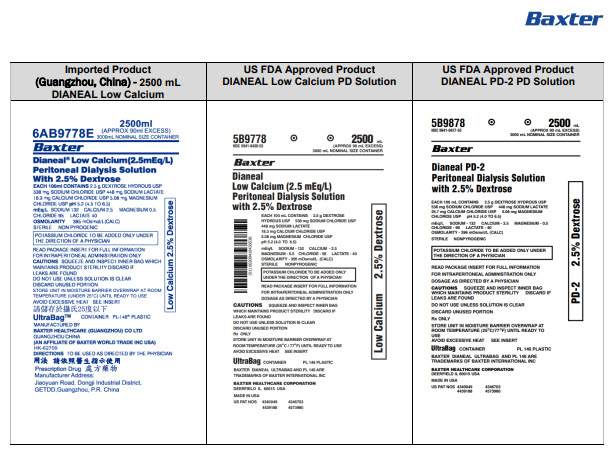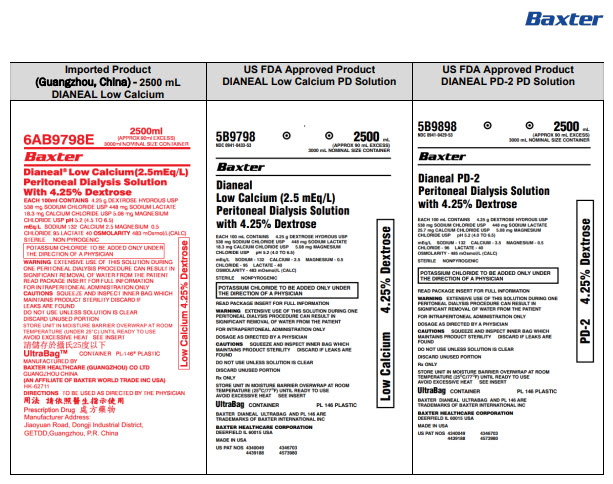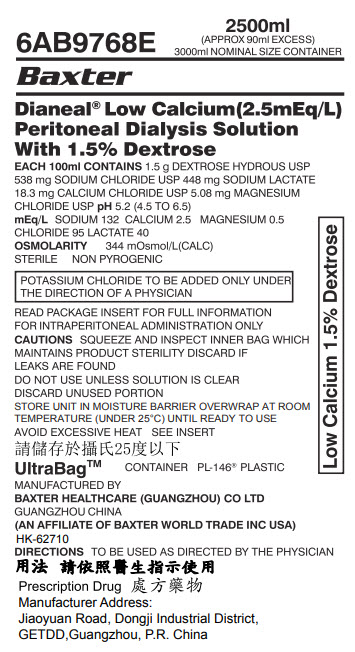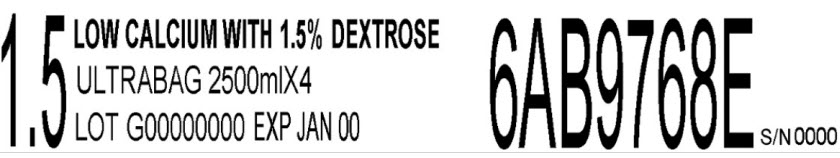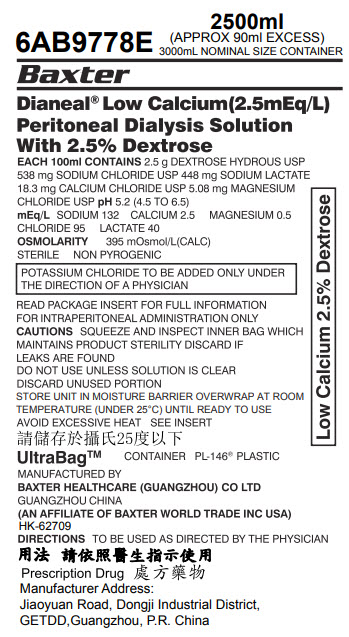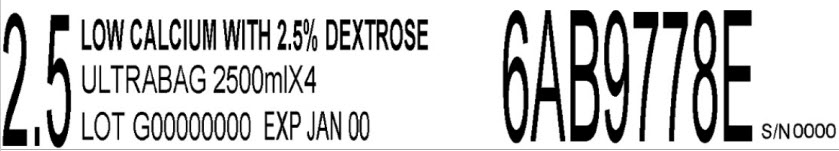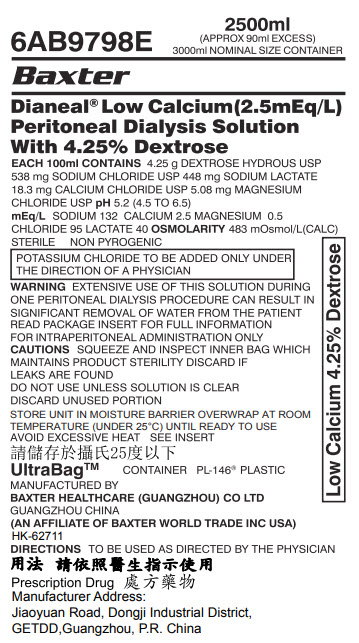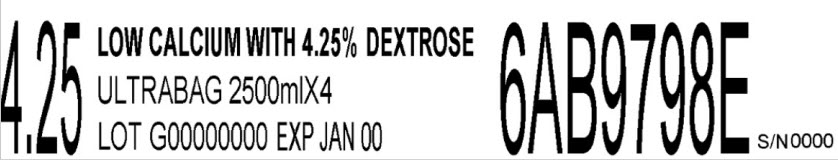 DRUG LABEL: DIANEAL LOW CALCIUM WITH DEXTROSE
NDC: 0941-0684 | Form: INJECTION, SOLUTION
Manufacturer: Vantive US Healthcare LLC
Category: prescription | Type: HUMAN PRESCRIPTION DRUG LABEL
Date: 20250509

ACTIVE INGREDIENTS: DEXTROSE MONOHYDRATE 1.5 g/100 mL; SODIUM CHLORIDE 538 mg/100 mL; SODIUM LACTATE 448 mg/100 mL; CALCIUM CHLORIDE 18.3 mg/100 mL; MAGNESIUM CHLORIDE 5.08 mg/100 mL
INACTIVE INGREDIENTS: WATER

DIANEAL Low Calcium with Dextrose

PACKAGE/LABEL PRINCIPAL DISPLAY PANEL

6AB9768E 2500ml
(APPROX 90ml EXCESS)
3000ml NOMINAL SIZE CONTAINER

BaxterLogo

Dianeal®Low Calcium(2.5mEq/L)
Peritoneal Dialysis Solution
With 1.5% Dextrose

EACH 100 ml CONTAINS1.5g DEXTROSE HYDROUS USP
538 mg SODIUM CHLORIDE USP 448 mg SODIUM LACTATE
18.3 mg CALCIUM CHLORIDE USP 5.08 mg MAGNESIUM
CHLORIDE USP pH5.2 (4.5 to 6.5)
mEq/LSODIUM 132 CALCIUM 2.5 MAGNESIUM 0.5
CHLORIDE 95 LACTATE 40
OSMOLARITY344 mOsmol/L(CALC)
STERILE NON PYROGENIC

POTASSIUM CHLORIDE TO BE ADDED ONLY UNDER
THE DIRECTION OF A PHYSICIAN

READ PACKAGE INSERT FOR FULL INFORMATION
FOR INTRAPERITONEAL ADMINISTRATION ONLY
CAUTIONSSQUEEZE AND INSPECT INNER BAG WHICH
MAINTAINS PRODUCT STERILITY DISCARD IF
LEAKS ARE FOUND
DO NOT USE UNLESS SOLUTION IS CLEAR
DISCARD UNUSED PORTION
STORE UNIT IN MOISTURE BARRIER OVERWRAP AT ROOM
TEMPERATURE (UNDER25°C) UNTIL READY TO USE
AVOID EXCESSIVE HEAT SEE INSERT

UltrabagTMCONTAINER PL-146 PLASTIC

MANUFACTURED BY
BAXTER HEALTHCARE (GUANGZHOU) CO LTD
GUANGZHOU CHINA
(AN AFFILIATE OF BAXTER WORLD TRADE INC USA)
HK-62710
DIRECTIONSTO BE USED AS DIRECTED BY THE PHYSICIAN

Prescription Drug
Manufacturer Address:
Jiaoyuan Road, Dongji Industrial District,
GETDD, Guangzhou, P.R. China

Low Calcium 1.5% Dextrose

1.5 LOW CALCIUM WITH 1.5% DEXTROSE
ULTRABAG 2500mlX4
LOT G00000000 EXP JAN 00

6AB9768E

S/N 0000

6AB9778E 2500ml
(APPROX 90ml EXCESS)
3000ml NOMINAL SIZE CONTAINER

BaxterLogo

Dianeal®Low Calcium(2.5mEq/L)
Peritoneal Dialysis Solution
With 2.5% Dextrose

EACH 100ml CONTAINS2.5g DEXTROSE HYDROUS USP
538 mg SODIUM CHLORIDE USP 448 mg SODIUM LACTATE
18.3 mg CALCIUM CHLORIDE USP 5.08 mg MAGNESIUM
CHLORIDE USP pH5.2 (4.5 to 6.5)
mEq/LSODIUM 132 CALCIUM 2.5 MAGNESIUM 0.5
CHLORIDE 95 LACTATE 40
OSMOLARITY395 mOsmol/L(CALC)
STERILE NON PYROGENIC

POTASSIUM CHLORIDE TO BE ADDED ONLY UNDER
THE DIRECTION OF A PHYSICIAN

READ PACKAGE INSERT FOR FULL INFORMATION
FOR INTRAPERITONEAL ADMINISTRATION ONLY
CAUTIONSSQUEEZE AND INSPECT INNER BAG WHICH
MAINTAINS PRODUCT STERILITY DISCARD IF
LEAKS ARE FOUND
DO NOT USE UNLESS SOLUTION IS CLEAR
DISCARD UNUSED PORTION
STORE UNIT IN MOISTURE BARRIER OVERWRAP AT ROOM
TEMPERATURE (UNDER25°C) UNTIL READY TO USE
AVOID EXCESSIVE HEAT SEE INSERT

UltrabagTMCONTAINER PL-146 PLASTIC

MANUFACTURED BY
BAXTER HEALTHCARE (GUANGZHOU) CO LTD
GUANGZHOU CHINA
(AN AFFILIATE OF BAXTER WORLD TRADE INC USA)
HK-62709
DIRECTIONSTO BE USED AS DIRECTED BY THE PHYSICIAN

Prescription Drug
Manufacturer Address:
Jiaoyuan Road, Dongji Industrial District,
GETDD, Guangzhou, P.R. China

Low Calcium 2.5% Dextrose

2.5 LOW CALCIUM WITH 2.5% DEXTROSE
ULTRABAG 2500mlX4
LOT G00000000 EXP JAN 00

6AB9778E

S/N 0000

6AB9798E 2500ml
(APPROX 90ml EXCESS)
3000ml NOMINAL SIZE CONTAINER

BaxterLogo

Dianeal®Low Calcium(2.5mEq/L)
Peritoneal Dialysis Solution
With 4.25% Dextrose

EACH 100ml CONTAINS4.25g DEXTROSE HYDROUS USP
538 mg SODIUM CHLORIDE USP 448 mg SODIUM LACTATE
18.3 mg CALCIUM CHLORIDE USP 5.08 mg MAGNESIUM
CHLORIDE USP pH5.2 (4.5 to 6.5)
mEq/LSODIUM 132 CALCIUM 2.5 MAGNESIUM 0.5
CHLORIDE 95 LACTATE 40 OSMOLARITY483 mOsmol/L(CALC)
STERILE NON PYROGENIC

POTASSIUM CHLORIDE TO BE ADDED ONLY UNDER
THE DIRECTION OF A PHYSICIAN

WARNINGEXTENSIVE USE OF THIS SOLUTION DURING
ONE PERITONEAL DIALYSIS PROCEDURE CAN RESULT IN
SIGNIFICANT REMOVAL OF WATER FROM THE PATIENT
READ PACKAGE INSERT FOR FULL INFORMATION
FOR INTRAPERITONEAL ADMINISTRATION ONLY
CAUTIONSSQUEEZE AND INSPECT INNER BAG WHICH
MAINTAINS PRODUCT STERILITY DISCARD IF
LEAKS ARE FOUND
DO NOT USE UNLESS SOLUTION IS CLEAR
DISCARD UNUSED PORTION
STORE UNIT IN MOISTURE BARRIER OVERWRAP AT ROOM
TEMPERATURE (UNDER25°C) UNTIL READY TO USE
AVOID EXCESSIVE HEAT SEE INSERT

UltrabagTMCONTAINER PL-146 PLASTIC

MANUFACTURED BY
BAXTER HEALTHCARE (GUANGZHOU) CO LTD
GUANGZHOU CHINA
(AN AFFILIATE OF BAXTER WORLD TRADE INC USA)
HK-62711
DIRECTIONSTO BE USED AS DIRECTED BY THE PHYSICIAN

Prescription Drug
Manufacturer Address:
Jiaoyuan Road, Dongji Industrial District,
GETDD, Guangzhou, P.R. China

Low Calcium 4.25% Dextrose

4.25 LOW CALCIUM WITH 4.25% DEXTROSE
ULTRABAG 2500mlX4
LOT G00000000 EXP JAN 00

6AB9798E

S/N 0000